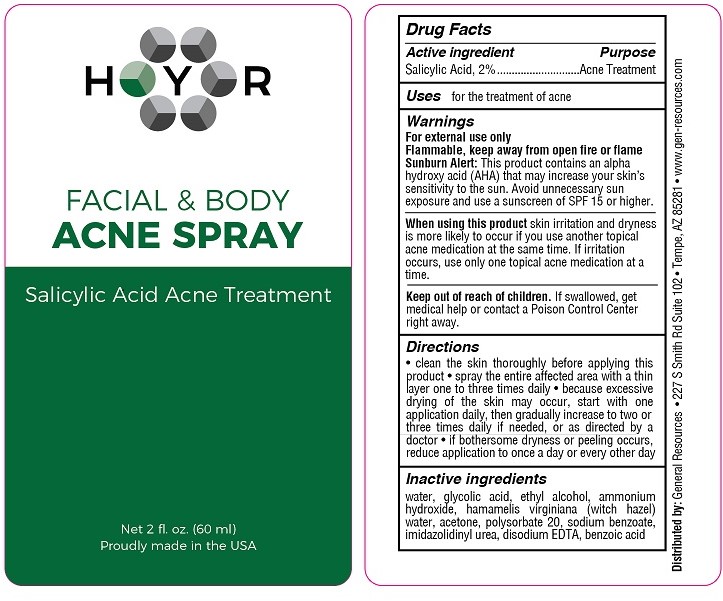 DRUG LABEL: HYR Facial and Body Acne
NDC: 70481-331 | Form: SPRAY
Manufacturer: General Resources LLC
Category: otc | Type: HUMAN OTC DRUG LABEL
Date: 20201018

ACTIVE INGREDIENTS: SALICYLIC ACID 2 g/100 mL
INACTIVE INGREDIENTS: BENZOIC ACID; EDETATE DISODIUM; WATER; ALCOHOL; WITCH HAZEL; SODIUM BENZOATE; POLYSORBATE 20; AMMONIA; ACETONE; GLYCOLIC ACID; IMIDUREA

HYR Facial & Body Acne Spray (Salicylic Acid)

Drug Facts

Active ingredient

Salicylic Acid, 2%

Purpose

Acne Treatment

Uses

for the treatment of acne

Warnings

For external use only.

Flammable, keep away from fire or flame.

Sunburn Alert: This product contains an alpha hydroxy acid (AHA) that may increase your skin's sensitivity to the sun. Avoid unnecessary sun exposure and use a sunscreen of SPF 15 or higher.

When using this product skin irritation and dryness is more likely to occur if you use another topical acne medication at the same time. If irritation occurs, only use one topical acne medication at a time.

Keep out of reach of children. If swallowed, get medical help or contact a Poison Control Center right away.

Directions

- clean the skin thoroughly before applying this product
- spray the entire affected area with a thin layer one to three times daily
- because excessive drying of the skin may occur, start with one application daily, then gradually increase to two or three times daily if needed or as directed by a doctor.
- if bothersome dryness or peeling occurs, reduce application to once a day or every other day.

INACTIVE INGREDIENT

Inactive ingredientswater, glycolic acid, ethyl alcohol, ammonium hydroxide, hamamelis virginiana (witch hazel) water, acetone, polysorbate 20, sodium benzoate, imidazolidinyl urea, disodium EDTA, benzoic acid

Distributed by: General Resources • 227 S Smith Rd Suite 102 • Tempe, AZ 85281 • www.gen-resources.com

PACKAGE LABEL

HYR

FACIAL & BODY

ACNE SPRAY

Salicylic Acid Acne Treatment

Net 2 fl. oz. (60 ml)

Proudly made in the USA